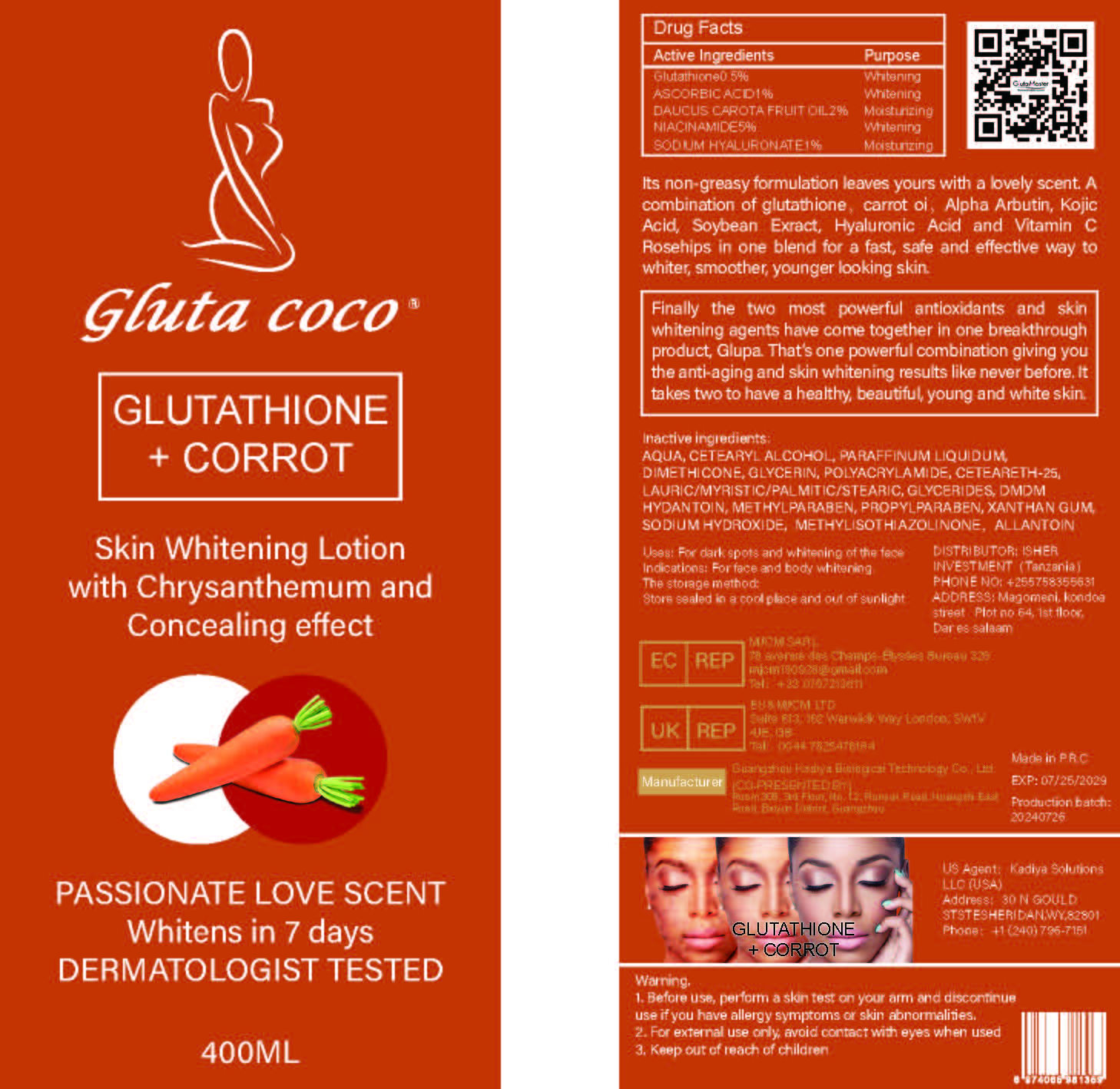 DRUG LABEL: GlutathioneSkinWhiteningLotion
NDC: 84423-061 | Form: EMULSION
Manufacturer: 713172913
Category: otc | Type: HUMAN OTC DRUG LABEL
Date: 20241217

ACTIVE INGREDIENTS: DAUCUS CAROTA SATIVA (CARROT) SEED OIL 4 g/400 mL; GLUTATHIONE 2 g/400 mL; ASCORBIC ACID 2 g/400 mL; NIACINAMIDE 20 g/400 mL
INACTIVE INGREDIENTS: PARAFFINUM LIQUIDUM; DMDM HYDANTOIN; AQUA; CETEARYL ALCOHOL; DIMETHICONE 1000; PROPYLPARABEN; SODIUM HYDROXIDE; METHYLISOTHIAZOLINONE; GLYCERIN; POLYACRYLAMIDE (10000 MW); ALLANTOIN; CETEARETH-25; METHYLPARABEN

PURPOSE

For body moisturisation and whitening

INACTIVE INGREDIENT

AQUA、CETEARYL ALCOHOL、PARAFFINUM LIQUIDUM、DIMETHICONE、GLYCERIN、POLYACRYLAMIDE、CETEARETH-25、LAURIC/MYRISTIC/PALMITIC/STEARIC、GLYCERIDES、DMDM HYDANTOIN、METHYLPARABEN、PROPYLPARABEN、XANTHAN GUM、SODIUM HYDROXIDE、 METHYLISOTHIAZOLINONE，ALLANTOIN

WARNINGS

1、For external use only, avoid contact with eyes when used
2、Keep out of reach of children

INDICATIONS AND USAGE

Its non-greasy formulation leaves yours with a lovely scent. A combination of glutathione, carrot oi, Alpha Arbutin, Kojic Acid, Soybean Exract, Hyaluronic Acid and Vitamin C Rosehips in one blend for a fast, safe and effective way to whiter, smoother, younger looking skin.

DOSAGE AND ADMINISTRATION

Finally the two most powerful antioxidants and skin whitening agents have come together in one breakthrough product, Glupa. That's one powerful combination giving you the anti-aging and skin whitening results like never before. It takes two to have a healthy, beautiful, young and white skin.

KEEP OUT OF REACH OF CHILDREN SECTION

Active Ingredients Purpose
Glutathione0.5% Whitening
ASCORBIC ACID1% Whitening
DAUCUS CAROTA FRUIT OIL2% Moisturizing
NIACINAMIDE5% Whitening
SODIUM HYALURONATE1% Moisturizing

PACKAGE LABEL

Active Ingredients Purpose
Glutathione0.5% Whitening
ASCORBIC ACID1% Whitening
DAUCUS CAROTA FRUIT OIL2% Moisturizing
NIACINAMIDE5% Whitening
SODIUM HYALURONATE1% Moisturizing

Uses：
For body moisturisation and whitening
The storage method：
Store sealed in a cool place and out of sunlight

Warning.
1、For external use only, avoid contact with eyes when used
2、Keep out of reach of children

Inactive ingredients：
AQUA、CETEARYL ALCOHOL、PARAFFINUM LIQUIDUM、DIMETHICONE、GLYCERIN、POLYACRYLAMIDE、CETEARETH-25、LAURIC/MYRISTIC/PALMITIC/STEARIC、GLYCERIDES、DMDM HYDANTOIN、METHYLPARABEN、PROPYLPARABEN、XANTHAN GUM、SODIUM HYDROXIDE、 METHYLISOTHIAZOLINONE，ALLANTOIN